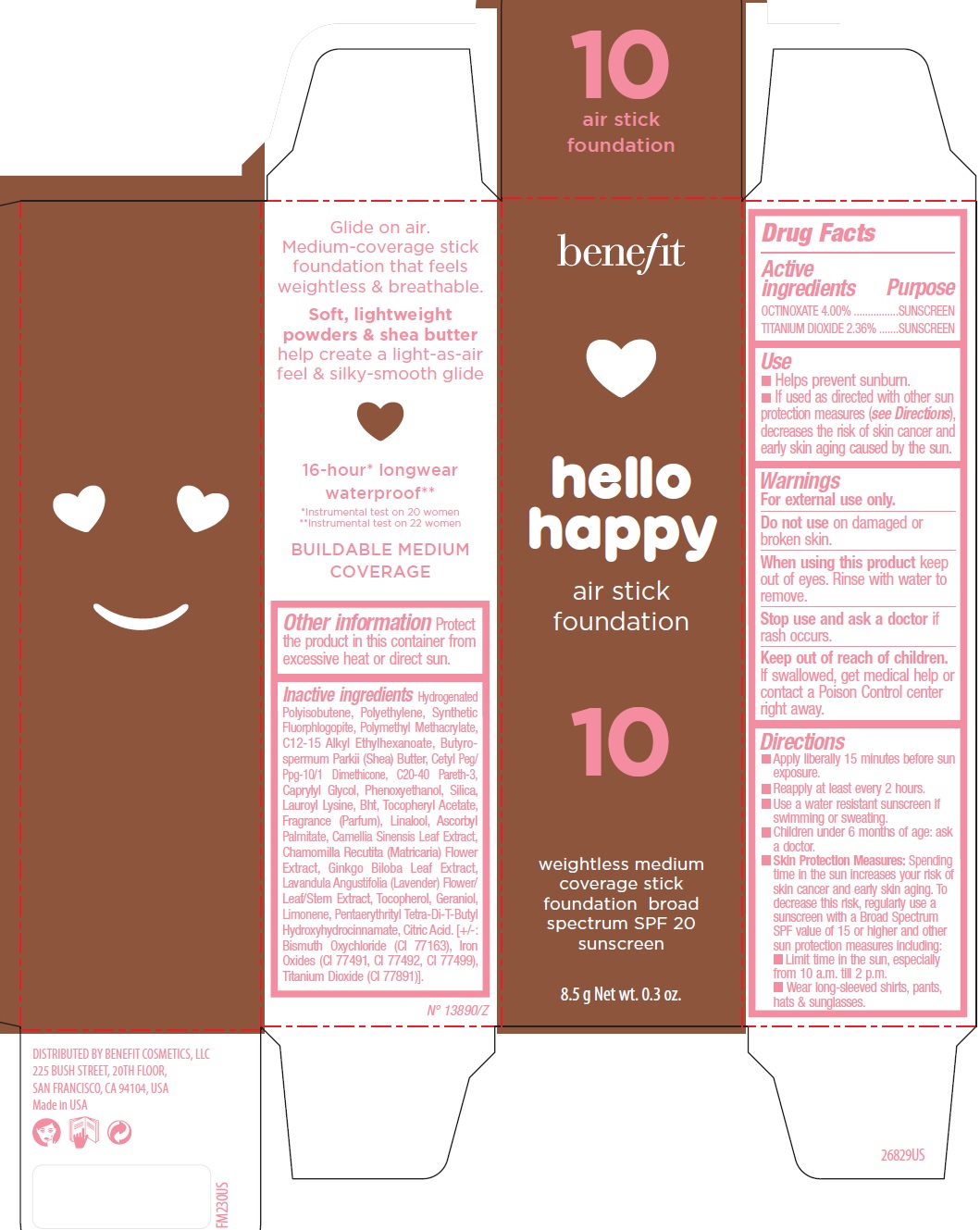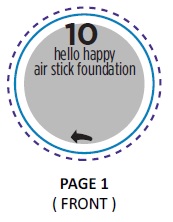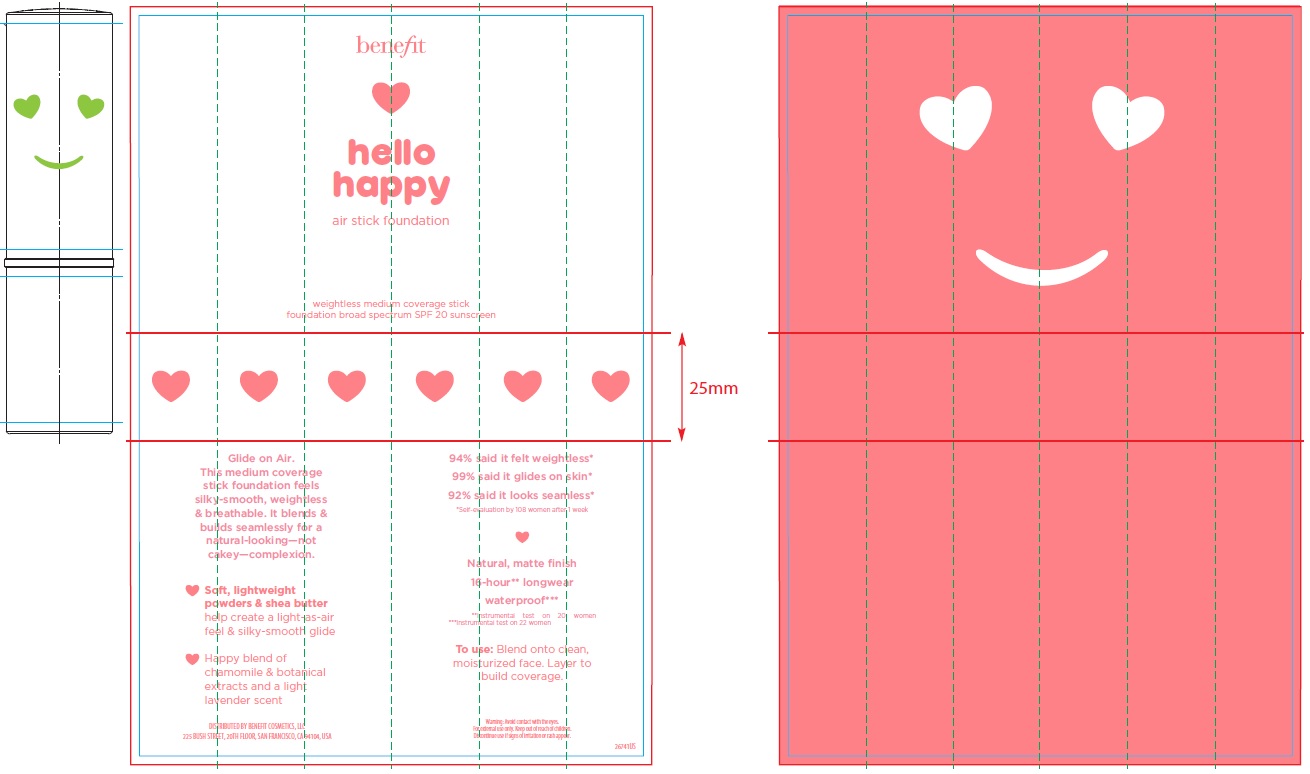 DRUG LABEL: Benefit Hello Happy Air Foundation

NDC: 66472-078 | Form: STICK
Manufacturer: Benefit Cosmetics, LLC
Category: otc | Type: HUMAN OTC DRUG LABEL
Date: 20200106

ACTIVE INGREDIENTS: OCTINOXATE 40 mg/1 g; TITANIUM DIOXIDE 23.6 mg/1 g
INACTIVE INGREDIENTS: HYDROGENATED POLYBUTENE (1300 MW); HIGH DENSITY POLYETHYLENE; POLY(METHYL METHACRYLATE; 450000 MW); C12-15 ALKYL ETHYLHEXANOATE; SHEA BUTTER; C20-40 PARETH-3; CAPRYLYL GLYCOL; PHENOXYETHANOL; SILICON DIOXIDE; LAUROYL LYSINE; BUTYLATED HYDROXYTOLUENE; .ALPHA.-TOCOPHEROL ACETATE; LINALOOL, (+/-)-; ASCORBYL PALMITATE; GREEN TEA LEAF; CHAMOMILE; GINKGO; TOCOPHEROL; GERANIOL; LIMONENE, (+)-; PENTAERYTHRITOL TETRAKIS(3-(3,5-DI-TERT-BUTYL-4-HYDROXYPHENYL)PROPIONATE); CITRIC ACID MONOHYDRATE; BISMUTH OXYCHLORIDE; FERRIC OXIDE RED; FERRIC OXIDE YELLOW; FERROSOFERRIC OXIDE

Benefit Hello Happy Air Stick Foundation Shade 10

Active ingredients

OCTINOXATE 4.00%

TITANIUM DIOXIDE 2.36%

Purpose

SUNSCREEN

Use

- Helps prevent sunburn.
- If used as directed with other sun protection measures (see Directions), decreases the risk of skin cancer and early skin aging caused by the sun.

Warnings

For external use only.

Do not use

on damaged or broken skin.

When using this product

keep out of eyes. Rinse with water to remove.

Stop use and ask a doctor

if rash occurs.

Keep out of reach of children.

If swallowed, get medical help or contact a Poison Control center right away.

Directions

- Apply liberally 15 minutes before sun exposure.
- Reapply at least every 2 hours.
- Use a water resistant sunscreen if swimming or sweating.
- Children under 6 months of age: ask a doctor.
- Skin Protection Measures: Spending time in the sun increases your risk of skin cancer and early skin aging. To decrease this risk, regularly use a sunscreen with a Broad Spectrum SPF value of 15 or higher and other sun protection measures including:
- Limit time in the sun, especially from 10 a.m. till 2 p.m.
- Wear long-sleeved shirts, pants, hats & sunglasses.

Other information

Protect the product in this container from excessive heat or direct sun.

Inactive ingredients

Hydrogenated Polyisobutene, Polyethylene, Synthetic Fluorphlogopite, Polymethyl Methacrylate, C12-15 Alkyl Ethylhexanoate, Butyrospermum Parkii (Shea) Butter, Cetyl Peg/ Ppg-10/1 Dimethicone, C20-40 Pareth-3, Caprylyl Glycol, Phenoxyethanol, Silica, Lauroyl Lysine, Bht, Tocopheryl Acetate, Fragrance (Parfum), Linalool, Ascorbyl Palmitate, Camellia Sinensis Leaf Extract, Chamomilla Recutita (Matricaria) Flower Extract, Ginkgo Biloba Leaf Extract, Lavandula Angustifolia (Lavender) Flower/ Leaf/Stem Extract, Tocopherol, Geraniol, Limonene, Pentaerythrityl Tetra-Di-T-Butyl Hydroxyhydrocinnamate, Citric Acid. [+/-: Bismuth Oxychloride (CI 77163), Iron Oxides (CI 77491, CI 77492, CI 77499), Titanium Dioxide (CI 77891)].